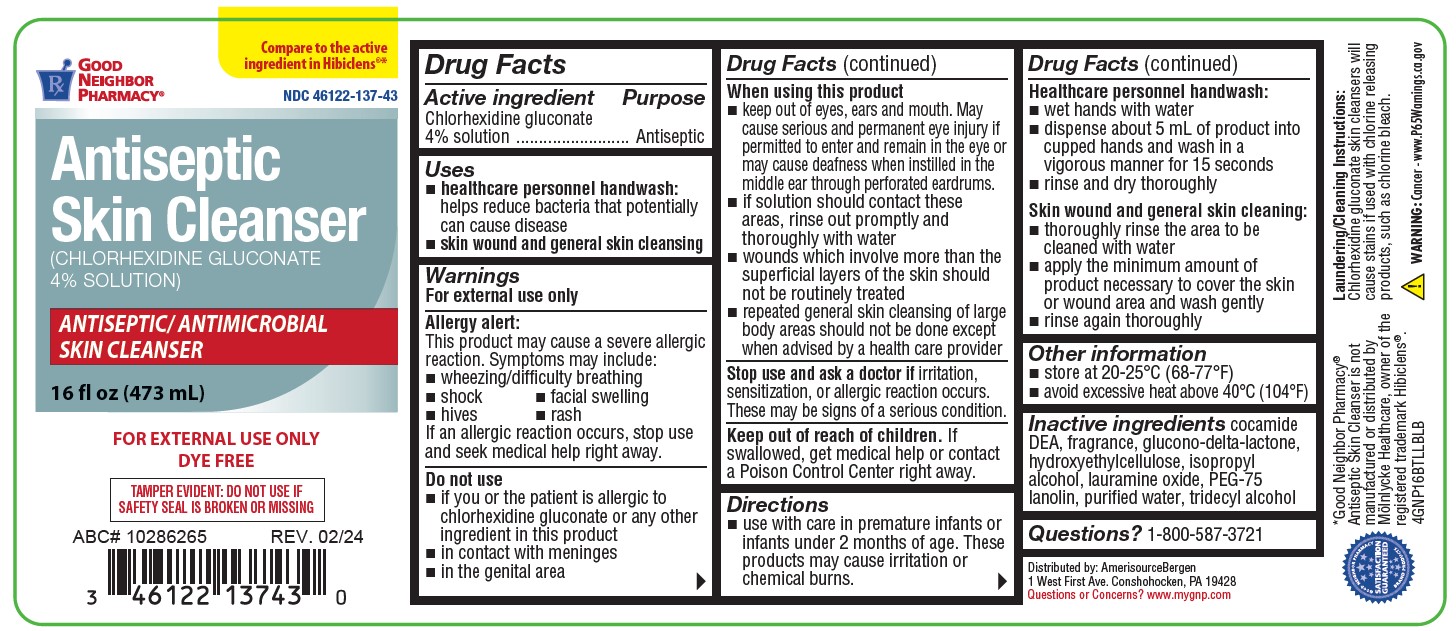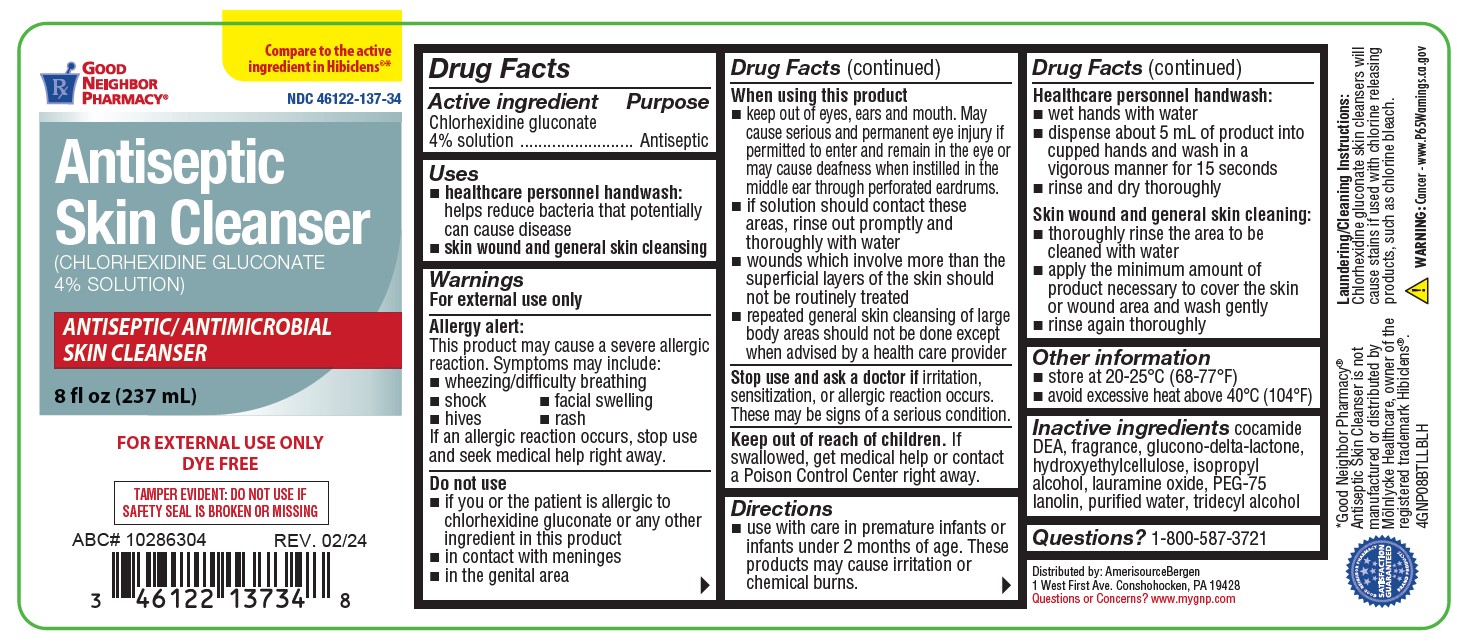 DRUG LABEL: Antiseptic Skin Cleanser
NDC: 46122-137 | Form: LIQUID
Manufacturer: AmerisourceBergen Drug Corporation
Category: otc | Type: HUMAN OTC DRUG LABEL
Date: 20251212

ACTIVE INGREDIENTS: CHLORHEXIDINE GLUCONATE 4 mg/100 mL
INACTIVE INGREDIENTS: COCO DIETHANOLAMIDE; PEG-75 LANOLIN; HYDROXYETHYL CELLULOSE (2000 CPS AT 1%); ISOPROPYL ALCOHOL; WATER; TRIDECYL ALCOHOL; GLUCONOLACTONE; LAURAMINE OXIDE

COMP Good Neighbor Pharmacy 8oz and 16oz

Active Ingredients

Chlorhexidine Gluconate 4% Solution

Purpose

Antiseptic

Uses

- healthcare personnel handwash: helps reduce bacteria that potentially can cause disease
- skin wound and general skin cleansing

Warnings

For external use only

Allergy alert: This product may cuase a severe allergic reaction. Symptoms may include:

- wheezing/difficulty breathing
- shock
- facial swelling
- hives
- rash

If an allergic reaction occurs, stop use and seek medical help right away.

Do not use

- if you or the patient is allergic to chlorhexidine gluconate or any other ingredient in this product
- in contact with meninges
- in the genital area

Keep out of reach of children

If swallowed, get medical help or contact a Poison Control Center right away.

Stop use and ask doctor if

irritation, sensitization, or allergic reaction occurs. These may be signs of a serious condition.

When using this product

- keep out of eyes, ears, and mouth. May cause serious and permanent eye injury if permitted to enter and remain in the eye or may cuase deafness when instilled in the middle ear through perforated eardrums.
- if solution should contact these areas, rinse out promptly and thoroughly with water
- wounds which involve more than the superficial layers of the skin should not be routinely treated
- repeated general skin cleansing of large body areas should not be done except when advised by a healthcare provider

Directions

- use with care in premature infants or infants under 2 months of age. These products may cause irritation or chemical burns.

Healthcare personnel handwash:

- wet hands with water
- dispense about 5ml of product into cupped hands and wash in vigorous manner for about 15 seconds
- rinse and dry thoroughly

Skin wound and normal skin cleansing:

- thoroughly rinse the area to be cleaned with water
- apply the minimum amount of product necessary to cover the skin or wound area and wash gently
- rinse again thoroughly

Other information

- store at 20°-25° C (68°-77° F)
- avoid excessive heat above 40° C (104° F)

Inactive ingredients

cocamide DEA, fragrance, glucono-delta-lactone, hydroxyethylcellulose, isopropyl alcohol, lauramine oxide, PEG-75 lanolin, purified water, tridecyl alcohol.

Questions of comments?

1-800-587-3721

OTHER SAFETY INFORMATION

Warning: This product contains a chemical (cocamide DEA) known to the State of California to cause cancer.

Laundering/Cleaning Instructions: Chlorhexidine gluconate skin cleansers will cause stains if used with chlorine releasing products. Rinse completely and use only non-chlorine detergents.

*Good Neighbor Pharmacy® Antiseptic Skin Cleanser is not manufactured or distributed by Mölnlycke Healthcare, owner of the registered trademark Hibiclens®.

Package label and principal display panel

Good Neighbor Pharmacy

NDC 46122-137-34

Antiseptic Skin Cleanser

(Chlorhexidine Gluconate 4% solution)

Antiseptic/Antimicrobial Skin Cleanser

8 FL OZ. (237 mL)

ABC# 10286304 REV. 02/24

FOR EXTERNAL USE ONLY

DYE FREE

TAMPER EVIDENT: DO NOT USE IF SAFETY SEAL IS BROKEN OR MISSING

Good Neighbor Pharmacy

Compare to the active ingredient in Hiniclens®*

NDC 46122-137-43

Antiseptic Skin Cleanser

(CHLORHEXIDINE GLUCONATE 4% SOLUTION)

ANTISEPTIC/ANTIMICROBIAL SKIN CLEANSER

16 fl oz (473 mL)

ABC#10286265 REV.02/24

FOR EXTERNAL USE ONLY

DYE FREE

TAMPER EVIDENT: DO NOT USE IF SAFETY SEAL IS BROKEN OR MISSING